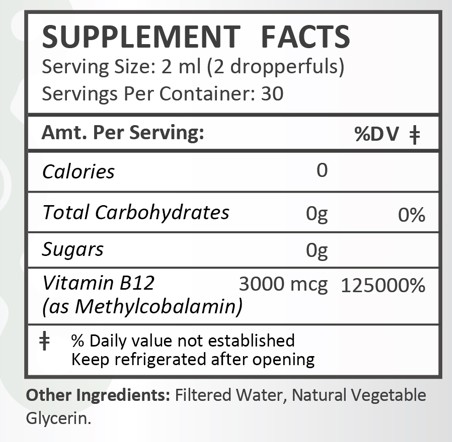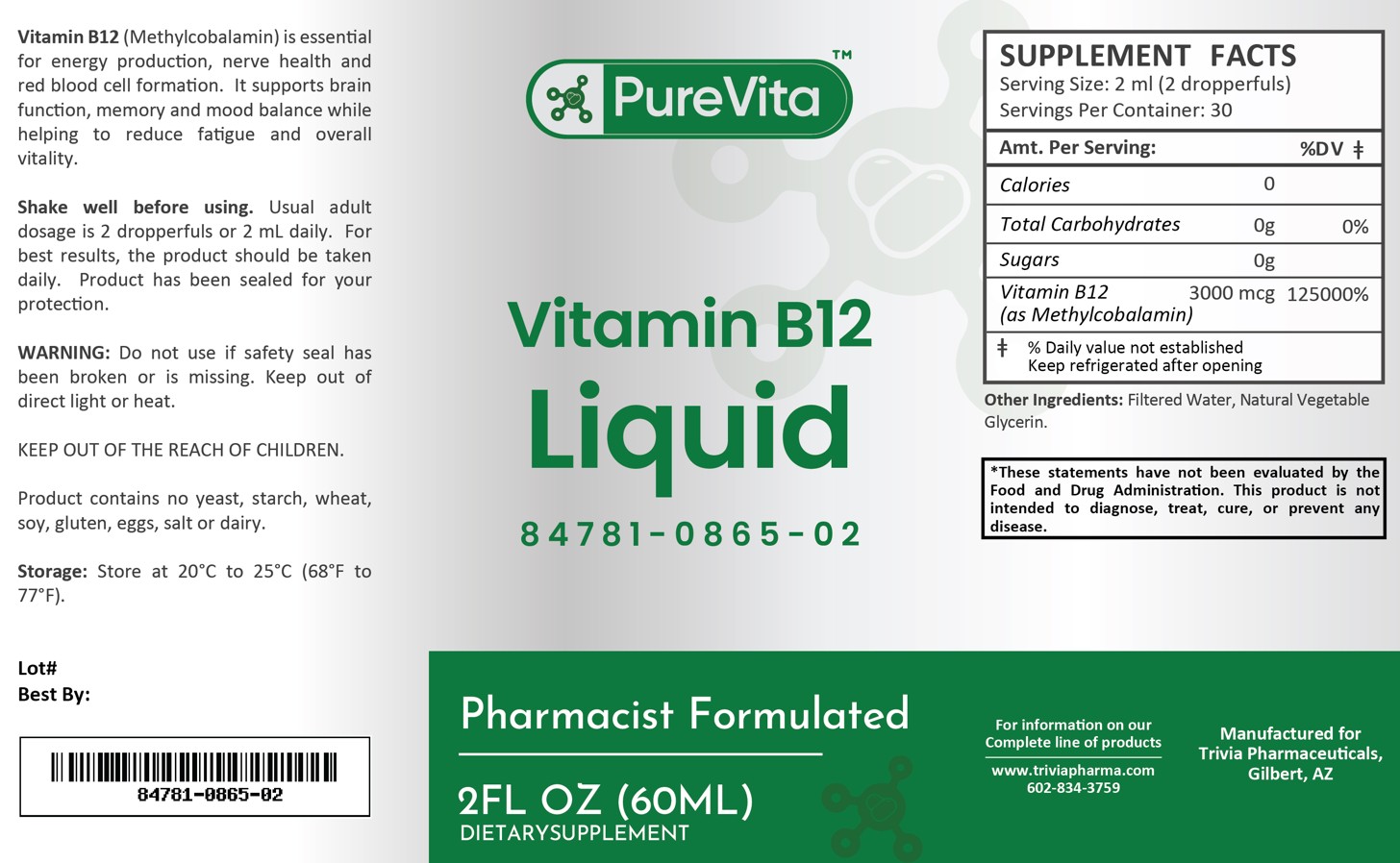 DRUG LABEL: PureVita Vitamin B12
NDC: 84781-865 | Form: LIQUID
Manufacturer: Trivia Pharmaceuticals
Category: other | Type: Dietary Supplement
Date: 20250217

ACTIVE INGREDIENTS: METHYLCOBALAMIN 3000 ug/2 mL

PureVita Vitamin B12

Health Claim:

PureVita Vitamin B12

Description:

PureVita Vitamin B12 (Methylcobalamin) is essential for energy production, nerve health and red blood cell formation. It supports brain function, memory, and mood balance while helping to reduce fatigue and overall vitality.

This listed product is not a National Drug Code, but instead has merely been formatted to comply with standard industry practice for pharmacy and insurance computer systems.

Warnings:

Do not use if safety seal has been broken or is missing. Keep out of direct light or heat.

KEEP OUT OF THE REACH OF CHILDREN.

Product contains no yeast, starch, wheat, soy, gluten, eggs, salt or dairy.

Dosage and Adminsitration:

Usual adult dose is 2 dropperfuls or 2 mL daily. For the best results, the product should be taken daily. Product has been sealed for your protection.

How Supplied:

PureVita Vitamin B12 Liquid is supplied as white, clear liquid.

84781-0865-02

Reserved for Professional Recommendation: All prescriptions using this product shall be pursuant to state statutes as applicable. This is not an Orange Book product. There are no implied or explicit claims on therapeutic equivalence.

Manufactured for:
Trivia Pharmaceuticals Gilbert, AZ

Storage:

Storage: Store at 20^0C to 25^0C (68^0F to 77^0F). Keep refrigerated after opening.